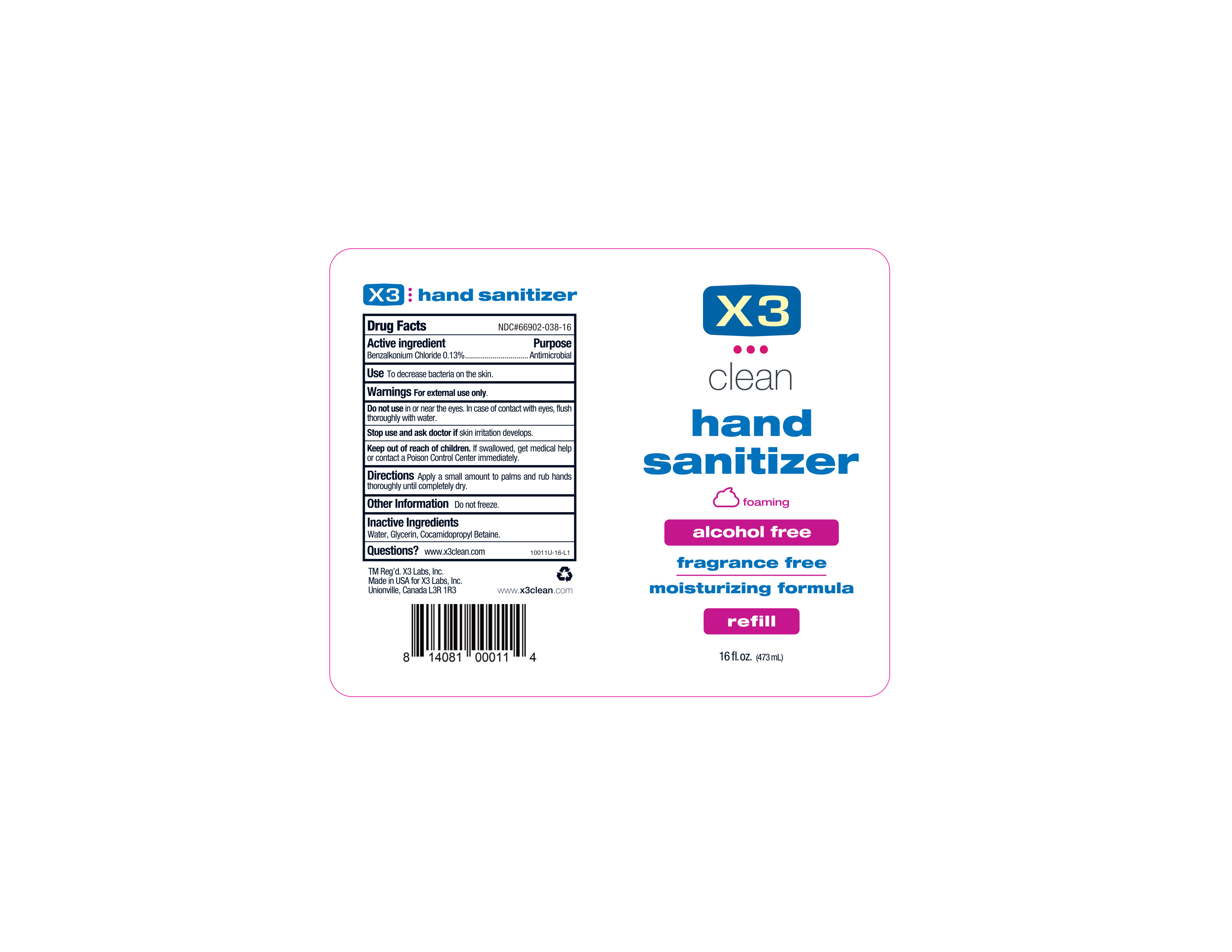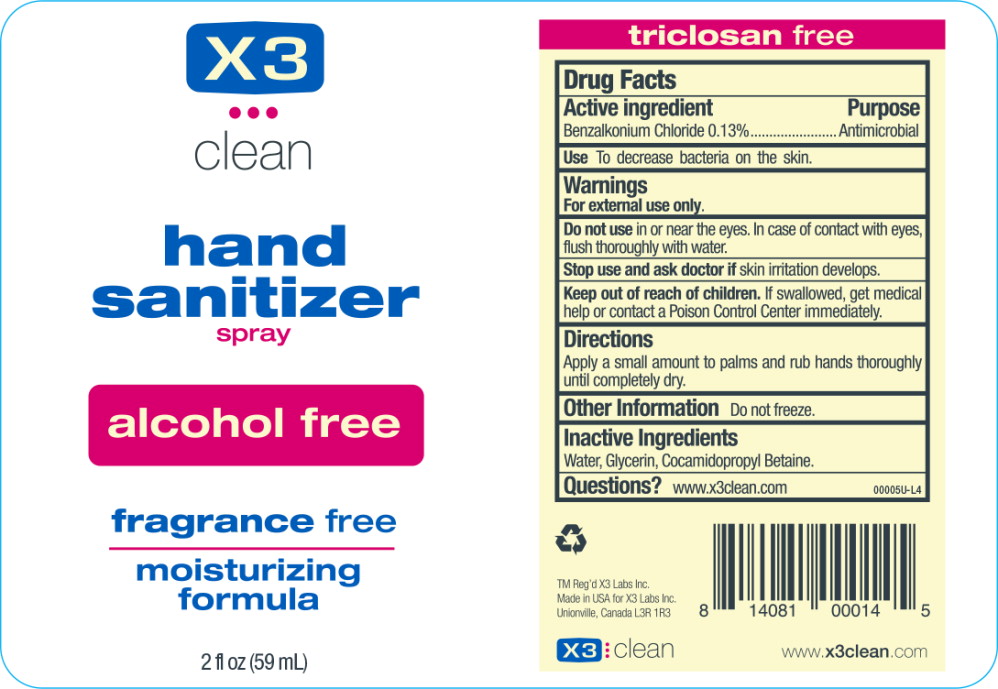 DRUG LABEL: X3 Clean Hand Sanitizer
NDC: 66902-038 | Form: LIQUID
Manufacturer: Natural Essentials, Inc.
Category: otc | Type: HUMAN OTC DRUG LABEL
Date: 20250715

ACTIVE INGREDIENTS: BENZALKONIUM CHLORIDE 1.3 mg/1 mL
INACTIVE INGREDIENTS: WATER; GLYCERIN; COCAMIDOPROPYL BETAINE

Drug Facts

Active ingredient

Benzalkonium Chloride 0.13%

Purpose

Antimicrobial

Use

To decrease bacteria on the skin.

Warnings

For external use only.

DO NOT USE

Do not usein or near the eyes. In case of contact with eyes, flush thoroughly with water.

Stop use and ask doctor ifskin irritation develops.

Keep out of reach of children.If swallowed, get medical help or contact a Poison Control Center immediately.

Directions

Apply a small amount to palms and rub hands thoroughly until completely dry.

Other Information

Do not freeze.

Inactive Ingredients

Water, Glycerin, Cocamidopropyl Betaine.

Questions?

www.x3clean.com

Principal Display Panel – 59 mL Bottle Label

X3

clean

hand
sanitizer
spray

alcohol free

fragrance free

moisturizing
formula

2 fl oz (59 mL)

Pricipal Display Panel - 16 fl oz (473 mL)

X3

Clean

Hand Sanitizer

Foaming

Alcohol Free

Fragrance Free

Moisturizing Formula

Refill

16 fl oz. (473 mL)